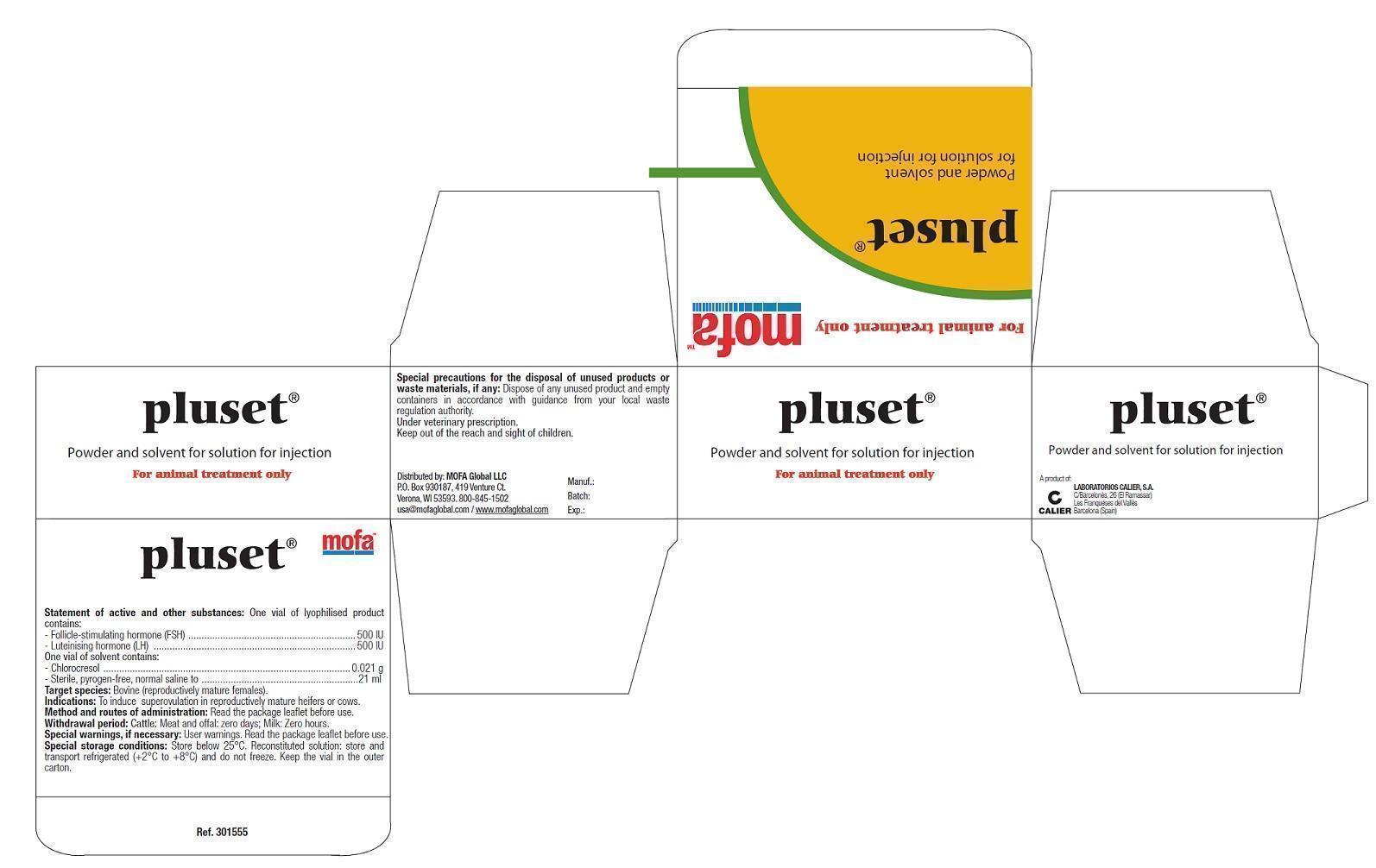 DRUG LABEL: PLUSET
NDC: 54129-178 | Form: KIT | Route: INTRAMUSCULAR
Manufacturer: Minitube of America, Inc.
Category: animal | Type: PRESCRIPTION ANIMAL DRUG LABEL
Date: 20150416

ACTIVE INGREDIENTS: Follitropin 50 [iU]/1 mL; Lutropin alfa 50 [iU]/1 mL
INACTIVE INGREDIENTS: Sodium Chloride; Water; CHLOROCRESOL 1 mg/1 mL

PLUSET Swine pituitary gonadotrophins

DESCRIPTION

PLUSET is a mixture of swine pituitary gonadotrophins used for the induction of multiple ovulations (superovulation). The use of standardized concentrations for both gonadotrophins guarantees a consistent quality of the product and eliminates possible variability in effectiveness from one lot to another. In the absence of an International Standard for the porcine gonadotrophin, dosing is carried out using the International Standard for human urine FSH and LH.

PROPERTIES AND ACTION

Ovarian stimulation with exogenous Follicle-Stimulating Hormone (FSH) allows a greater number of ova to be produced than normally produced in a single reproductive cycle.

The pituitary hormone extract contains variable levels of Follicle-Stimulating Hormone (FSH) and Luteinizing Hormone (LH).

Clearly in order to obtain proper and effective superovulation which provides satisfactory results involving a high number of living embryos, it is necessary to carry out a treatment that guarantees the activation and progress of multiple follicle maturation in the most "physiological" and repeatable way possible.

Thus, given that it influences the activity of FSH, it is important to have a defined level of LH present.

PLUSET is manufactured in a method chosen to ensure that the defined level of LH content is consistently mantained.

Kinetic studies of FSH and LH in the bloodstream of bovine has shown a half-life of 150 minutes for FSH and a half-life of 40 minutes for LH.

ANIMAL SPECIES AND INDICATIONS

To induce superovulation in reproductively mature heifers or cows.

CONTRA-INDICATIONS

Do not use in pregnant animals.

WARNINGS

Special warnings

The following recommendations for the use of PLUSET for the induction of superovulation with adequate response should be followed:

a.The donor animal must have had at least one normal oestrous cycle prior to the initiation of PLUSET treatment.

b.The donor animal should not have any signs of clinical illness when treatment with PLUSET begins. Ovarian examination should confirm the presence of a functional corpus luteum and the absence of any pathological conditions such as cystic ovarian degeneration or adhesions around the ovaries.

c.Treatment should be initiated between day 9 and 12 of the oestrous cycle (with day 11 generally giving best results).

d. A luteolytic dose of prostaglandin F2 alpha or analogue should be given intramuscularly at 60 and/or 72 hours after the beginning of superovulation treatment.

e.Standing oestrus will take place 40-48 h after prostaglandin treatment and animals should be bred 12 h after the onset of standing heat and, again 12 h later with high quality semen.

f. Following the non-surgical recovery of embryos on day 7, it is recommended to give the animals another prostaglandin treatment to assure a rapid return to heat; if not, animals should be examined 4 weeks after, to ascertain that normal ovarian activity has been restored. Breeding can take place at the first heat after superovulation, which normally is seen after 28 days.

g.The effect of repeated treatments with PLUSET over long periods has not been assessed for all possible schedule treatment Therefore it is recommended that PLUSET not be administered more than twice for superovulation and that at least one natural oestrus cycle be allowed to occur between the two superovulation treatments.

h.The interval from calving to initiation of superovulation treatment should be at least 3 months.

i.Individually variability of responses depending of age, breed, on reproductive status, could occur.

User warnings

Care should be taken when handling the product to avoid self-injection. Accidental self-injection may cause biological effects in women and to the unborn child. In the event of accidental self-injection in women who are pregnant, or whose pregnancy status is unknown, seek medical advice.

Do not use during pregnancy

A slight reduction in milk yield has been observed during superovulatory heat (as in other heats) but the production in general reaches pretreatment levels within 2 weeks.

It is not advisable to exceed the maximum recommended dose. High doses of FSH and LH could be associated with reduced fertilisation rate, resulting in an increase of unfertilised embryos.

DOSAGE AND ADMINISTRATION ROUTE

Dissolve each vial of freeze-dried product with 10.5 ml of solvent.

Use aseptic technique during reconstitution and when removing aliquots from the vial. Adequately clean and disinfect the vial closure prior to each entry with a sterile needle.

Mix gently during reconstitution.

PLUSET is to be given by intramuscular injection only.

The following treatment schedule is recommended for the induction of superovulation in the cow:

The total recommended dose is 800 to 1000 IU in decreasing doses for 4 to 5 days. Considering the variability between animals and taking into account breed, age and reproductive status the dosing schedule should be adjusted appropriately. It is therefore recommended to seek veterinary advice on appropriate dosing patterns. For heifers and beef cows a total dose of 800 IU is recommended. For dairy cows the dose could be increased to 1000 IU taking into account increasing age, parity number and dairy production.

Recommended schedule for 800 IU in 4 days:

Day 1* | 08:00 hrs | 3.0 ml i.m. | (150 IU FSH + 150 IU LH)
 | 20:00 hrs | 3.0 ml i.m. | (150 IU FSH + 150 IU LH)
Day 2 | 08:00 hrs | 2.5 ml i.m. | (125 IU FSH + 125 IU LH)
 | 20:00 hrs | 2.5 ml i.m. | (125 IU FSH + 125 IU LH)
Day 3** | 08:00 hrs | 1.5 ml i.m. | (75 IU FSH + 75 IU LH)
 | 20:00 hrs | 1.5 ml i.m | (75 IU FSH + 75 IU LH)
Day 4 | 08:00 hrs | 1.0 ml i.m. | (50 IU FSH + 50 IU LH)
 | 20:00 hrs | 1.0 ml i.m. | (50 IU FSH + 50 IU LH)

Recommended schedule for 1000 IU in 5 days:

Day 1* | 08:00 hrs | 3.0 ml i.m. | (150 IU FSH + 150 IU LH)
 | 20:00 hrs | 3.0 ml i.m. | (150 IU FSH + 150 IU LH)
Day 2 | 08:00 hrs | 2.5 ml i.m. | (125 IU FSH + 125 IU LH)
 | 20:00 hrs | 2.5 ml i.m. | (125 IU FSH + 125 IU LH)
Day 3** | 08:00 hrs | 2.0 ml i.m. | (100 IU FSH + 100 IU LH)
 | 20:00 hrs | 2.0 ml i.m | (100 IU FSH + 100 IU LH)
Day 4 | 08:00 hrs | 1.5 ml i.m. | (75 IU FSH + 75 IU LH)
 | 20:00 hrs | 1.5 ml i.m. | (75 IU FSH + 75 IU LH)
Day 5 | 08:00 hrs | 1.0 ml i.m. | (50 IU FSH + 50 IU LH)
 | 20:00 hrs | 1.0 ml i.m. | (50 IU FSH + 50 IU LH)

* Corresponds to the 11th day of the oestrus cycle.

** A luteolytic dose of prostaglandin F2 alpha should be administered intramuscularly at 60 and/or 72 hours after the beginning of superovulation treatment.

STORAGE

Keep out of the reach and sight of children. Store below 25ºC. Reconstituted solution: store and transport refrigerated (+2ºC to +8ºC) and do not freeze. Keep the vial in the outer carton. Do not use after the expiry date stated on the label and carton after EXP. Shelf life after reconstitution according to directions: six days.

CONTENTS

Cardboard box with 2 glass vials of 10 ml of lyophilised product and 1 glass vial of 21 ml of diluent.